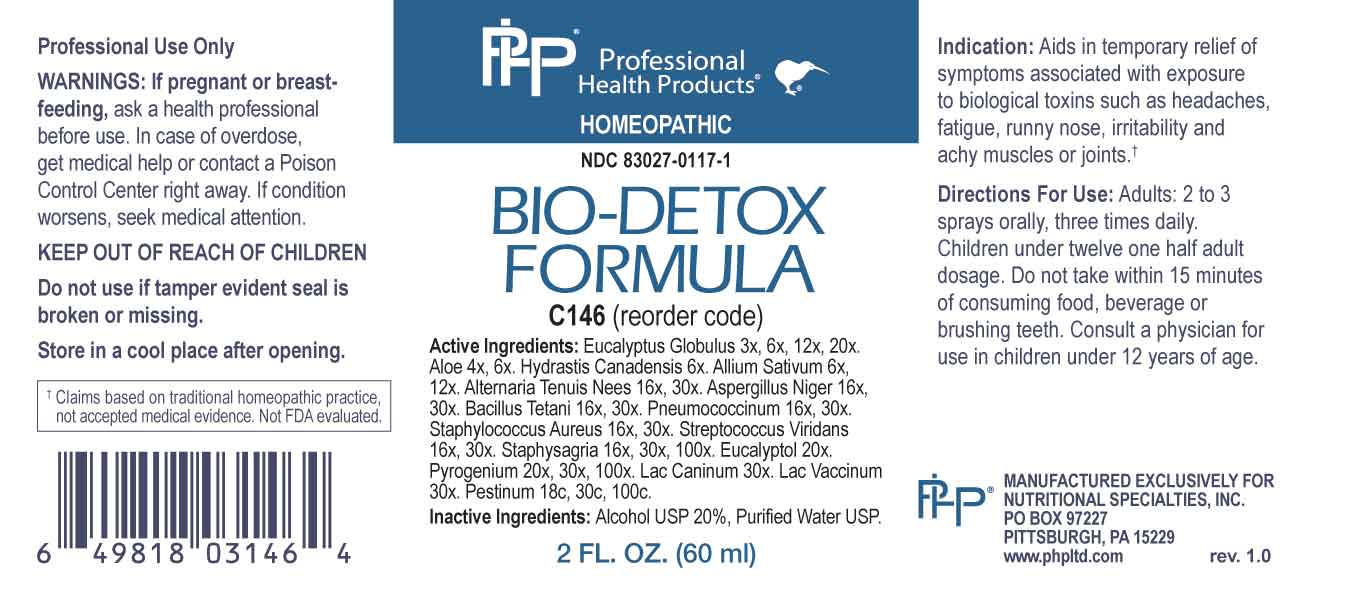 DRUG LABEL: Bio Detox Formula
NDC: 83027-0117 | Form: SPRAY
Manufacturer: Nutritional Specialties, Inc.
Category: homeopathic | Type: HUMAN OTC DRUG LABEL
Date: 20231009

ACTIVE INGREDIENTS: EUCALYPTUS GLOBULUS LEAF 3 [hp_X]/1 mL; ALOE 4 [hp_X]/1 mL; GOLDENSEAL 6 [hp_X]/1 mL; GARLIC 6 [hp_X]/1 mL; ALTERNARIA ALTERNATA 16 [hp_X]/1 mL; ASPERGILLUS NIGER VAR. NIGER 16 [hp_X]/1 mL; CLOSTRIDIUM TETANI 16 [hp_X]/1 mL; STREPTOCOCCUS PNEUMONIAE 16 [hp_X]/1 mL; STAPHYLOCOCCUS AUREUS 16 [hp_X]/1 mL; STREPTOCOCCUS VIRIDANS GROUP 16 [hp_X]/1 mL; DELPHINIUM STAPHISAGRIA SEED 16 [hp_X]/1 mL; EUCALYPTOL 20 [hp_X]/1 mL; RANCID BEEF 20 [hp_X]/1 mL; CANIS LUPUS FAMILIARIS MILK 30 [hp_X]/1 mL; COW MILK 30 [hp_X]/1 mL; YERSINIA PESTIS 18 [hp_C]/1 mL
INACTIVE INGREDIENTS: WATER; ALCOHOL

DRUG FACTS:

ACTIVE INGREDIENTS:

Eucalyptus Globulus 3X, 6X, 12X, 20X, Aloe 4X, 6X, Hydrastis Canadensis 6X, Allium Sativum 6X, 12X, Alternaria Tenuis Nees 16X, 30X, Aspergillus Niger 16X, 30X, Bacillus Tetani 16X, 30X, Pneumococcinum 16X, 30, Staphylococcus Aureus 16X, 30X, Streptococcus Viridans 16X, 30X, Staphysagria 16X, 30X, 100X, Eucalyptol 20X, Pyrogenium 20X, 30X, 100X, Lac Caninum 30X, Lac Vaccinum 30X, Pestinum 18C, 30C, 100C.

PURPOSE:

Aids in temporary relief of symptoms associated with exposure to biological toxins such as headaches, fatigue, runny nose, irritability and achy muscles or joints.†

†Claims based on traditional homeopathic practice, not accepted medical evidence. Not FDA evaluated.

WARNINGS:

Professional Use Only

If pregnant or breast-feeding, ask a health professional before use.

In case of overdose, get medical help or contact a Poison Control Center right away.

If condition worsens, seek medical attention.

KEEP OUT OF REACH OF CHILDREN

Do not use if tamper evident seal is broken or missing.

Store in a cool place after opening

KEEP OUT OF REACH OF CHILDREN:

In case of overdose, get medical help or contact a Poison Control Center right away.

DIRECTIONS:

Adults: 2 to 3 sprays orally, three times daily. Children under twelve one half adult dosage. Do not take within 15 minutes of consuming food, beverage or brushing teeth. Consult a physician for use in children under 12 years of age.

INDICATIONS:

Aids in temporary relief of symptoms associated with exposure to biological toxins such as headaches, fatigue, runny nose, irritability and achy muscles or joints.†

†Claims based on traditional homeopathic practice, not accepted medical evidence. Not FDA evaluated.

INACTIVE INGREDIENTS:

Alcohol USP 20%, Purified Water USP.

QUESTIONS:

MANUFACTURED EXCLUSIVELY FOR

NUTRITIONAL SPECIALTIES, INC.

PO BOX 97227

PITTSBURG, PA 15229

www.phpltd.com

PACKAGE LABEL DISPLAY:

Professional

Health Products

HOMEOPATHIC

NDC 83027-0117-1

BIO-DETOX

FORMULA

2 FL. OZ (60 ml)